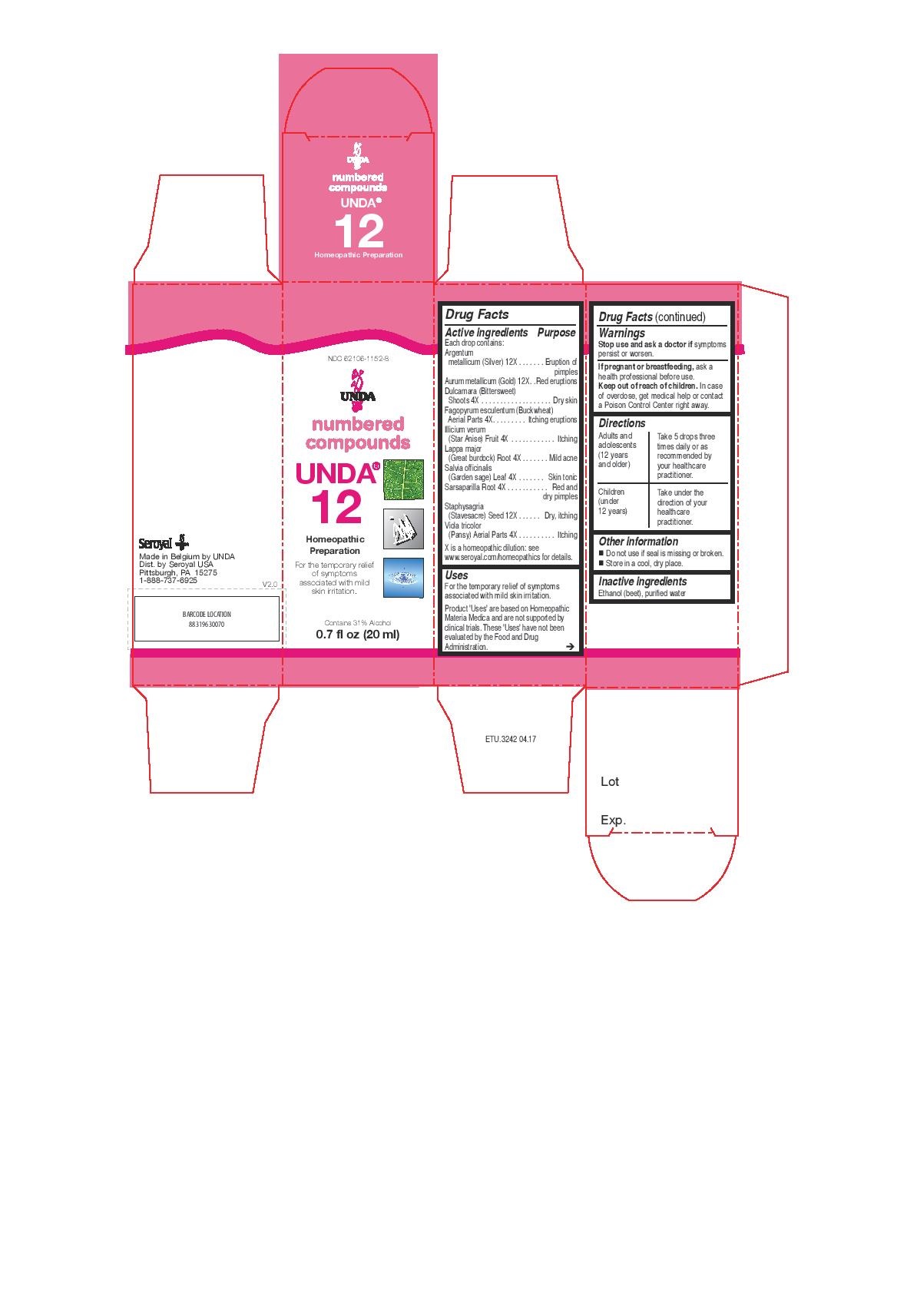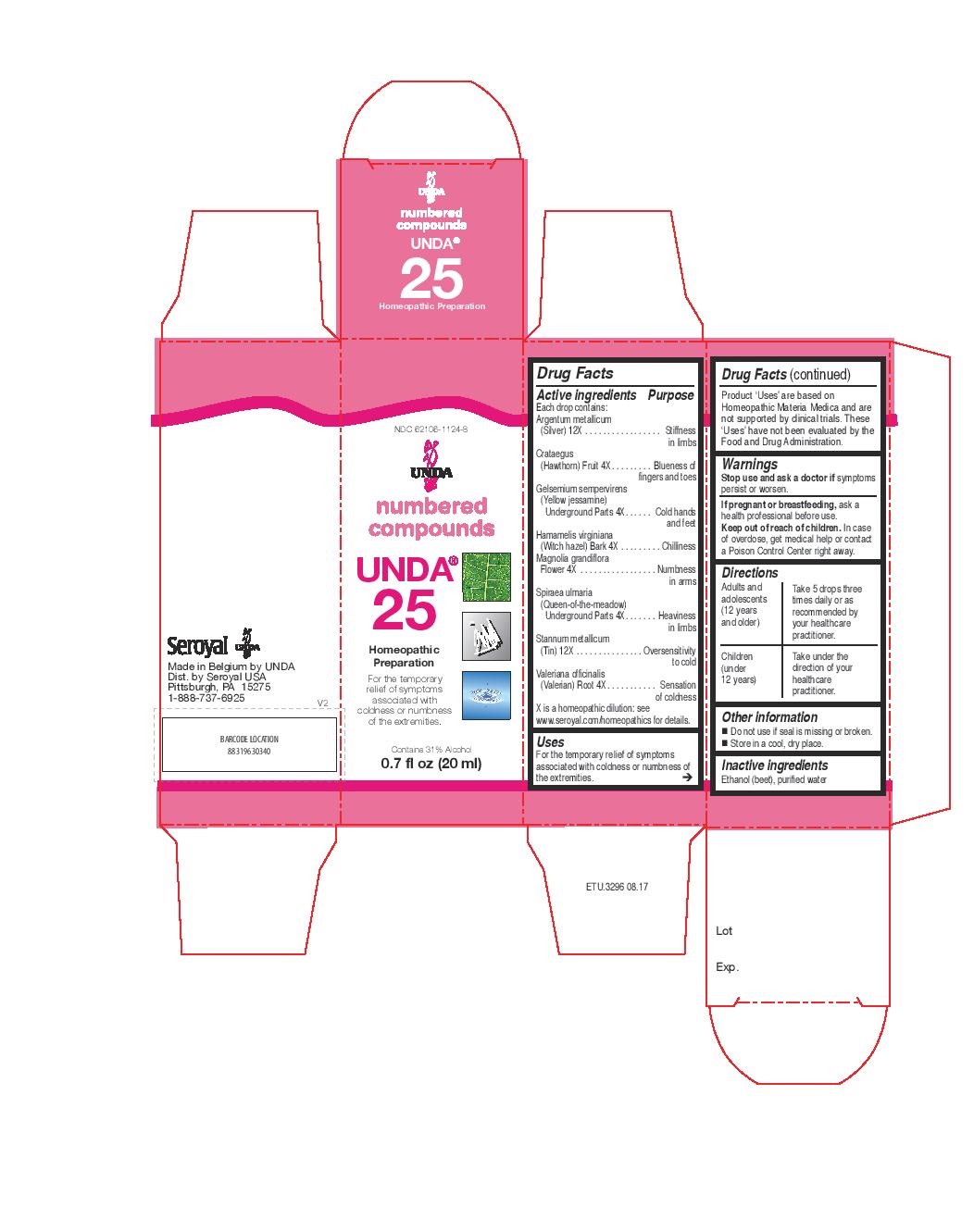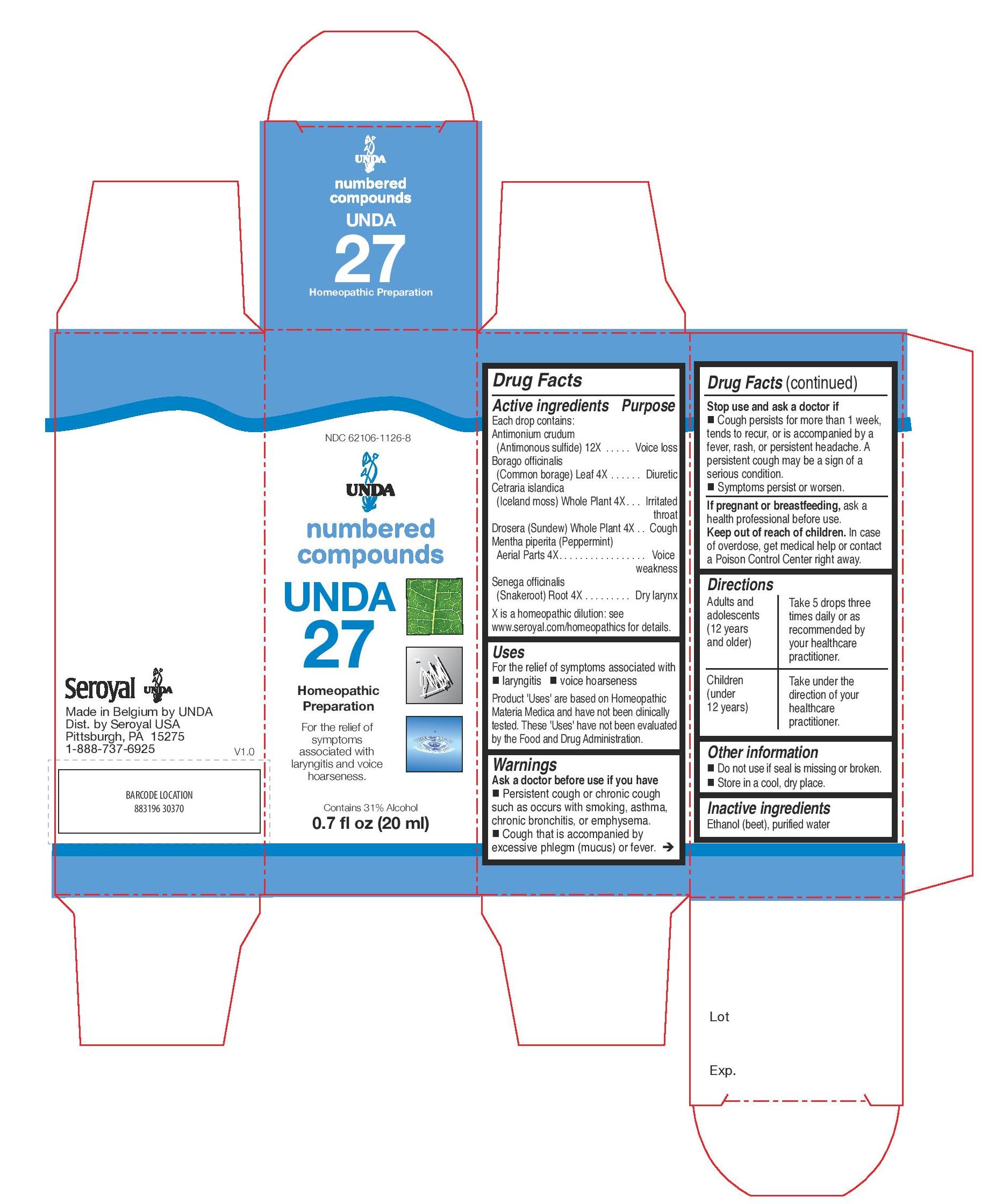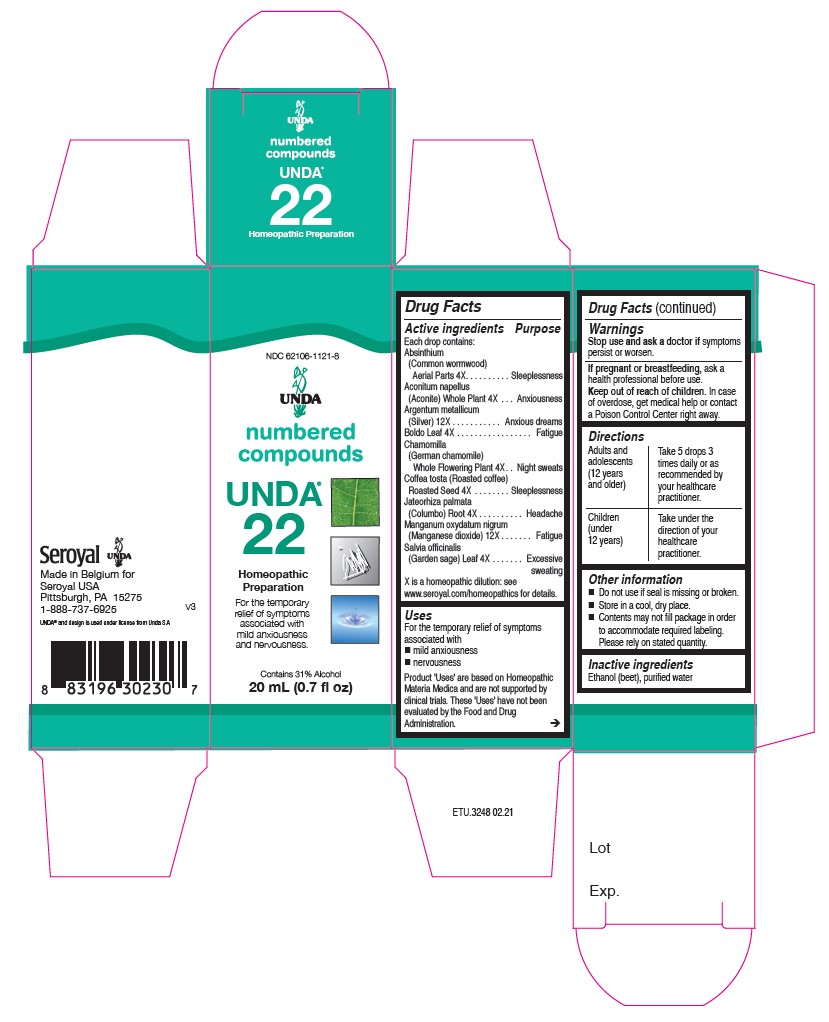 DRUG LABEL: UNDA 25
NDC: 62106-1124 | Form: LIQUID
Manufacturer: Seroyal USA
Category: homeopathic | Type: HUMAN OTC DRUG LABEL
Date: 20210715

ACTIVE INGREDIENTS: SILVER 12 [hp_X]/20 mL; FILIPENDULA ULMARIA ROOT 4 [hp_X]/20 mL; CRATAEGUS FRUIT 4 [hp_X]/20 mL; TIN 12 [hp_X]/20 mL; VALERIAN 4 [hp_X]/20 mL; GELSEMIUM SEMPERVIRENS ROOT 4 [hp_X]/20 mL; HAMAMELIS VIRGINIANA BARK 4 [hp_X]/20 mL; MAGNOLIA GRANDIFLORA FLOWER 4 [hp_X]/20 mL
INACTIVE INGREDIENTS: ALCOHOL; WATER

UNDA Numbers

Active ingredients

Each drop contains:

Argentum metallicum (Silver) 12X
Aurum metallicum (Gold) 12X
Dulcamara (Bittersweet) Shoots 4X
Fagopyrum esculentum Aerial Parts 4X
Illicium verum (Star Anise) Fruit 4X
Lappa major (Great burdock) Root 4X
Salvia officinalis (Garden sage) Leaf 4X
Sarsaparilla Root 4X
Staphysagria (Stavesacre) Seed 12X
Viola tricolor (Pansy) Aerial Parts 4X

Uses

For the temporary relief of symptoms associated with mild skin irritation.

Warnings

Stop use and ask a doctor if symptoms persist or worsen.

If pregnant or breastfeeding, ask a health professional before use.
Keep out of reach of children.

In case of overdose, get medical help or contact a Poison Control Center right away.

Stop use and ask a doctor if symptoms persist or worsen.

PREGNANCY OR BREAST FEEDING

If pregnant or breastfeeding, ask a health professional before use.

Keep out of reach of children.

OVERDOSAGE

In case of overdose, get medical help or contact a Poison Control Center right away.

Inactive ingredients
Ethanol (beet), purified water

Other information

Do not use if seal is missing or broken.

Store in a cool, dry place.

Directions

Adults and adolescents (12 years and older): Take 5 drops three times daily or as
recommended by your healthcare practitioner.

Children (under 12 years): Take under the direction of your
healthcare practitioner.

Uses

For the temporary relief of symptoms associated with mild skin irritation.

Directions
Adults and adolescents (12 years and older): Take 5 drops three times daily or as
recommended by your healthcare practitioner.
Children (under 12 years): Take under the direction of your
healthcare practitioner.

Active ingredients

Each drop contains:

Absinthium (Common wormwood) Aerial Parts 4X
Aconitum napellus (Aconite) Whole Plant 4X
Argentum metallicum (Silver) 12X
Boldo Leaf 4X
Chamomilla (German chamomile) Whole Flowering Plant 4X
Coffea tosta (Roasted coffee) Seed 4X
Jateorhiza palmata (Columbo) Root 4X
Manganum oxydatum nigrum (Manganese dioxide) 12X
Salvia officinalis (Garden sage) Leaf 4X

Uses
For the temporary relief of symptoms associated with mild anxiousness and nervousness.

Warnings
Stop use and ask a doctor if symptoms persist or worsen.

If pregnant or breastfeeding, ask a health professional before use.
Keep out of reach of children.

In case of overdose, get medical help or contact a Poison Control Center right away.

Stop use and ask a doctor if symptoms persist or worsen.

PREGNANCY OR BREAST FEEDING

If pregnant or breastfeeding, ask a health professional before use.

Keep out of reach of children.

OVERDOSAGE

In case of overdose, get medical help or contact a Poison Control Center right away.

Inactive ingredients
Ethanol (beet), purified water

Other information
Do not use if seal is missing or broken.
Store in a cool, dry place.

Contents may not fill package in order
to accommodate required labeling.
Please rely on stated quantity.

Directions
Adults and adolescents (12 years and older): Take 5 drops three times daily or as
recommended by your healthcare practitioner.
Children (under 12 years): Take under the direction of your
healthcare practitioner.

Uses
For the temporary relief of symptoms associated with mild anxiousness and nervousness.

Directions
Adults and adolescents (12 years and older): Take 5 drops three times daily or as
recommended by your healthcare practitioner.
Children (under 12 years): Take under the direction of your
healthcare practitioner.

Active ingredients

Each drop contains:
Argentum metallicum (Silver) 12X
Crataegus (Hawthorn) Fruit 4X
Gelsemium sempervirens (Yellow jessamine) Underground Parts 4X
Hamamelis virginiana (Witch hazel) Bark 4X
Magnolia grandiflora Flower 4X
Spiraea ulmaria (Queen-of-the-meadow) Underground Parts 4X
Stannum metallicum (Tin) 12X
Valeriana officinalis (Valerian) Root 4X

Uses
For the temporary relief of symptoms associated with
coldness or numbness of the extremities.

Warnings
Stop use and ask a doctor if symptoms persist or worsen.
If pregnant or breastfeeding, ask a health professional before use.
Keep out of reach of children.
In case of overdose, get medical help or contact a Poison Control Center right away.

Stop use and ask a doctor if symptoms persist or worsen.

PREGNANCY OR BREAST FEEDING

If pregnant or breastfeeding, ask a health professional before use.

Keep out of reach of children.

OVERDOSAGE

In case of overdose, get medical help or contact a Poison Control Center right away.

Inactive ingredients
Ethanol (beet), purified water

Directions
Adults and adolescents (12 years and older): Take 5 drops three times daily or as
recommended by your healthcare practitioner.
Children (under 12 years): Take under the direction of your
healthcare practitioner.

Uses
For the temporary relief of symptoms associated with
coldness or numbness of the extremities.

Directions
Adults and adolescents (12 years and older): Take 5 drops three times daily or as
recommended by your healthcare practitioner.
Children (under 12 years): Take under the direction of your
healthcare practitioner.

Other information
Do not use if seal is missing or broken.
Store in a cool, dry place.

Active ingredients

Each drop contains:
Antimonium crudum (Antimonous sulfide) 12X
Borago officinalis (Common borage) Leaf 4X
Cetraria islandica (Iceland moss) Whole Plant 4X
Drosera (Sundew) Whole Plant 4X
Mentha piperita (Peppermint) Aerial Parts 4X
Senega officinalis (Snakeroot) Root 4X

Uses
For the relief of symptoms associated with laryngitis and voice hoarseness.

Warnings

Ask a doctor before use if you have Persistent cough or chronic cough
such as occurs with smoking, asthma, chronic bronchitis, or emphysema and Cough that is accompanied by
excessive phlegm (mucus) or fever.

Stop use and ask a doctor if symptoms persist or worsen and Cough persists for more than 1 week,
tends to recur, or is accompanied by a fever, rash, or persistent headache. A persistent cough may be a sign of a serious condition.
If pregnant or breastfeeding, ask a health professional before use.
Keep out of reach of children.
In case of overdose, get medical help or contact a Poison Control Center right away.

Stop use and ask a doctor if symptoms persist or worsen and Cough persists for more than 1 week,

tends to recur, or is accompanied by a fever, rash, or persistent headache. A persistent cough may be a sign of a serious condition.

PREGNANCY OR BREAST FEEDING

If pregnant or breastfeeding, ask a health professional before use.

Keep out of reach of children.

OVERDOSAGE

In case of overdose, get medical help or contact a Poison Control Center right away.

Ask a doctor before use if you have Persistent cough or chronic cough
such as occurs with smoking, asthma, chronic bronchitis, or emphysema and Cough that is accompanied by
excessive phlegm (mucus) or fever.

Inactive ingredients
Ethanol (beet), purified water

Other information
Do not use if seal is missing or broken.
Store in a cool, dry place.

Directions
Adults and adolescents (12 years and older): Take 5 drops three times daily or as
recommended by your healthcare practitioner.
Children (under 12 years): Take under the direction of your
healthcare practitioner.

Uses
For the relief of symptoms associated with laryngitis and voice hoarseness.

Directions
Adults and adolescents (12 years and older): Take 5 drops three times daily or as
recommended by your healthcare practitioner.
Children (under 12 years): Take under the direction of your
healthcare practitioner.

PACKAGE LABEL

NDC 62106-1152-8

UNDA

numbered compounds

UNDA 12

Homeopathic Preparation

For the temporary relief of symptoms

associated with mild skin irritation.

Contains 31% Alcohol
0.7 fl oz (20 ml)

PACKAGE LABEL

NDC 62106-1121-8

UNDA
numbered compounds
UNDA 22
Homeopathic Preparation

For the temporary relief of symptoms
associated with mild anxiousness
and nervousness.
Contains 31% Alcohol
0.7 fl oz (20 ml)

PACKAGE LABEL

NDC 62106-1124-8

UNDA
numbered compounds
UNDA 25
Homeopathic Preparation

For the temporary relief of symptoms
associated with coldness or numbness
of the extremities.
Contains 31% Alcohol
0.7 fl oz (20 ml)

PACKAGE LABEL

UNDA
NDC 62106-1126-8
numbered compounds
UNDA 27
Homeopathic Preparation

For the relief of symptoms associated with laryngitis and voice hoarseness.
Contains 31% Alcohol
0.7 fl oz (20 mL)